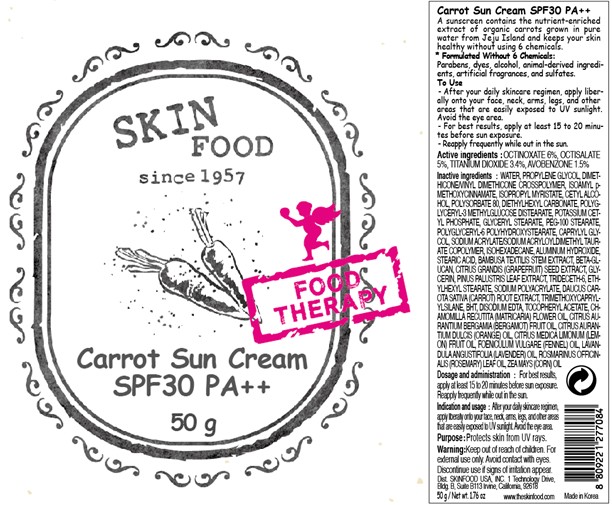 DRUG LABEL: CARROT SUN
NDC: 76214-014 | Form: CREAM
Manufacturer: SKINFOOD CO., LTD.
Category: otc | Type: HUMAN OTC DRUG LABEL
Date: 20110907

ACTIVE INGREDIENTS: OCTINOXATE 3 g/50 g; OCTISALATE 2.5 g/50 g; TITANIUM DIOXIDE 1.7 g/50 g; AVOBENZONE 0.75 g/50 g
INACTIVE INGREDIENTS: WATER; PROPYLENE GLYCOL; ISOPROPYL MYRISTATE; CETYL ALCOHOL; POLYSORBATE 80; DIETHYLHEXYL CARBONATE; POTASSIUM CETYL PHOSPHATE; GLYCERYL MONOSTEARATE; PEG-100 STEARATE; CAPRYLYL GLYCOL; ISOHEXADECANE; ALUMINUM HYDROXIDE; STEARIC ACID; GLYCERIN; PINUS PALUSTRIS POLLEN; CARROT; TRIMETHOXYCAPRYLYLSILANE; BUTYLATED HYDROXYTOLUENE; EDETATE DISODIUM; CHAMOMILE FLOWER OIL; BERGAMOT OIL; CITRUS SINENSIS FLOWER OIL; CITRUS LIMON FRUIT OIL; FENNEL OIL; LAVENDER OIL; ROSEMARY OIL; STARCH, CORN

Drug Facts

ACTIVE INGREDIENT

Active ingredients: OCTINOXATE 6%, OCTISALATE 5%, TITANIUM DIOXIDE 3.4%, AVOBENZONE 1.5%

Inactive ingredients:
WATER, PROPYLENE GLYCOL, DIMETHICONE/VINYL DIMETHICONE CROSSPOLYMER, ISOAMYL p-METHOXYCINNAMATE, ISOPROPYL MYRISTATE, CETYL ALCOHOL, POLYSORBATE 80, DIETHYLHEXYL CARBONATE, POLYGLYCERYL-3 METHYLGLUCOSE DISTEARATE, POTASSIUM CETYL PHOSPHATE, GLYCERYL STEARATE, PEG-100 STEARATE, POLYGLYCERYL-6 POLYHYDROXYSTEARATE, CAPRYLYL GLYCOL, SODIUM ACRYLATE/SODIUM ACRYLOYLDIMETHYL TAURATE COPOLYMER, ISOHEXADECANE, ALUMINUM HYDROXIDE, STEARIC ACID, BAMBUSA TEXTILIS STEM EXTRACT, BETA-GLUCAN, CITRUS GRANDIS (GRAPEFRUIT) SEED EXTRACT, GLYCERIN, PINUS PALUSTRIS LEAF EXTRACT, TRIDECETH-6, ETHYLHEXYL STEARATE, SODIUM POLYACRYLATE, DAUCUS CAROTA SATIVA (CARROT) ROOT EXTRACT, TRIMETHOXYCAPRYLYLSILANE, BHT, DISODIUM EDTA, TOCOPHERYL ACETATE, CHAMOMILLA RECUTITA (MATRICARIA) FLOWER OIL, CITRUS AURANTIUM BERGAMIA (BERGAMOT) FRUIT OIL, CITRUS AURANTIUM DULCIS (ORANGE) OIL, CITRUS MEDICA LIMONUM (LEMON) FRUIT OIL, FOENICULUM VULGARE (FENNEL) OIL, LAVANDULA ANGUSTIFOLIA (LAVENDER) OIL, ROSMARINUS OFFICINALIS (ROSEMARY) LEAF OIL, ZEA MAYS (CORN) OIL

Purpose: Protects skin from UV rays.

Warnings:
For external use only. Avoid contact with eyes.
Discontinue use if signs of irritation appear.

Keep out of reach of children:
Keep out of reach of children.

Indication and usage:
After your daily skincare regimen, apply liberally onto your face, neck, arms, legs, and other areas that are easily exposed to UV sunlight. Avoid the eye area.

Dosage and administration:
For best results, apply at least 15 to 20 minutes before sun exposure.
Reapply frequently while out in the sun.